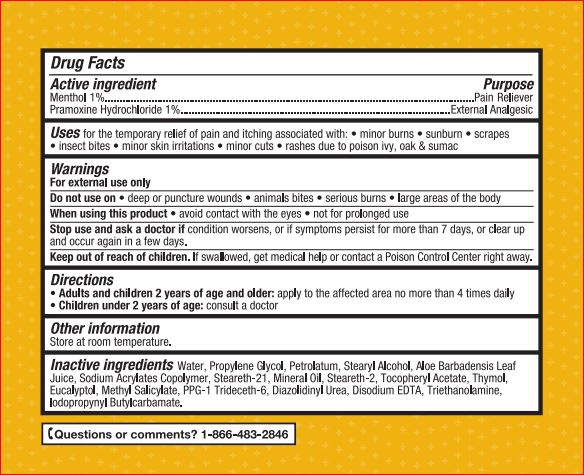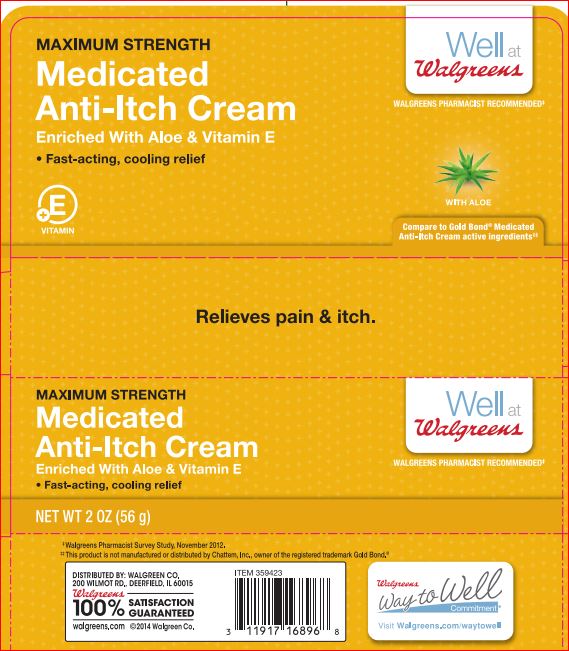 DRUG LABEL: MEDICATED ANTI-ITCH
NDC: 0363-3231 | Form: CREAM
Manufacturer: Walgreens
Category: otc | Type: HUMAN OTC DRUG LABEL
Date: 20180215

ACTIVE INGREDIENTS: Menthol 1 g/100 g; Pramoxine Hydrochloride 1 g/100 g
INACTIVE INGREDIENTS: Water; Propylene Glycol; Petrolatum; Stearyl Alcohol; ALOE VERA LEAF; Steareth-21; Mineral Oil; Steareth-2; .ALPHA.-TOCOPHEROL ACETATE; Thymol; Eucalyptol; Methyl Salicylate; PPG-1 Trideceth-6; Diazolidinyl Urea; EDETATE DISODIUM; TROLAMINE; Iodopropynyl Butylcarbamate

Drug Facts

Active ingredients Purpose

Menthol – 1.00% Pain Reliever
Pramoxine Hydrochloride – 1.00% External Analgesic

INDICATIONS AND USAGE

Uses For temporarily relief of pain and itching associated with:• sunburn • minor burns • scrapes • insect bites • minor skin irritation • minor cuts • rashes due to poison ivy, oak & sumac

Warnings For external use only

Do not use on • deep or puncture wounds • animal bites • serious burns • large areas of the body

When using this product • Avoid contact with eyes • not for prolonged use

Stop use and ask a doctor if

• condition worsens
• symptoms persisit more than 7 days or clear up and occur again within a few days

KEEP OUT OF REACH OF CHILDREN

Keep out of reach of the children. If product is swallowed, get medical help or contact a Poison Control Center right away

Directions

- Adults and children 2 years of age and older: apply to the affected area no more than 4 times daily
- Children under 2 years of age: consult a doctor

Other information

Store at room temperature.

Inactive ingredients

Water, Propylene Glycol, Petrolatum, Stearyl Alcohol, Aloe Barbadensis Leaf Juice, Sodium Acrylates Copolymer, Steareth-21, Mineral Oil,
Steareth-2, Tocopheryl Acetate, Thymol, Eucalyptol, Methyl Salicylate, PPG-1 Trideceth-6, Diazolidinyl Urea, Disodium EDTA, Triethanolamine,
Iodopropynyl Butylcarbamate